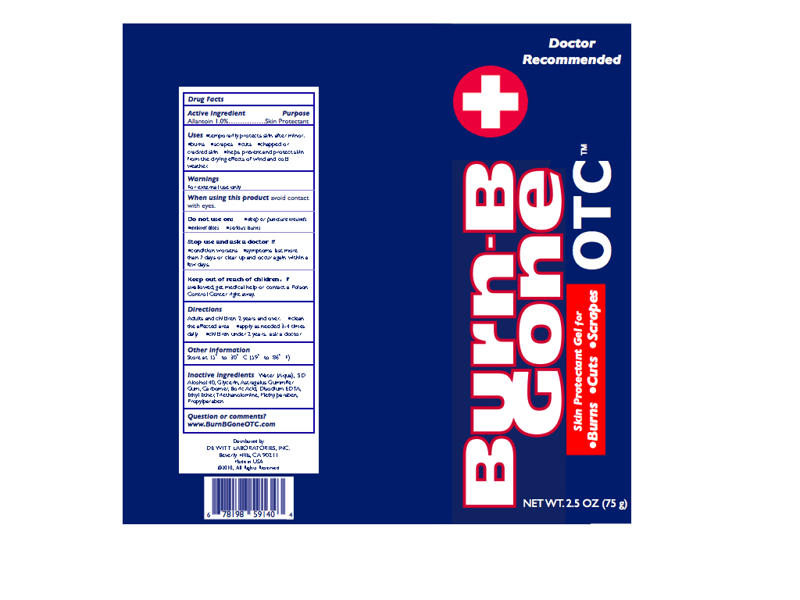 DRUG LABEL: Burn-B Gone OTC
NDC: 51483-002 | Form: GEL
Manufacturer: DeWitt Laboratories, Inc
Category: otc | Type: HUMAN OTC DRUG LABEL
Date: 20100601

ACTIVE INGREDIENTS: Allantoin 0.75 g/75 g
INACTIVE INGREDIENTS: Water; Alcohol; Glycerin; Tragacanth; Carbomer Homopolymer Type C; Boric Acid; Edetate Disodium; Ether; Trolamine; Methylparaben; Propylparaben

Burn-B Gone OTC 75g Tube

Active Ingredient: Allantoin 1.0%

Purpose: Skin Protectant

Uses:
Temporarily protects skin after minor

- burns
- scrapes
- cuts

- Helps prevent, temporarily protects, and helps relieve chapped or cracked skin.

- Helps prevent and protect skin from the drying effects of wind and cold weather.

Warnings:

For External Use Only

When using this product avoid contact with eyes.

Do not use on

- deep or puncture wounds
- animal bites
- serious burns

Stop use and ask a doctor if

- condition worsens
- symptoms persist for more than 7 days or clear up and occur again within a few days.

Keep out of reach of children. If swallowed, get medical help or contact a Poison Control Center right away.

Directions:

- Adults and children 2 years of age and older - Cleanse affected area thoroughly. Apply 3-4 times daily.
- Children under 2 years old - Consult a doctor.

Other Information: Store between 15-30C (59-86F)

INACTIVE INGREDIENT

Inactive Ingredients: Water (Aqua), SD Alcohol 40, Glycerin, Astragalus Gummifer Gum, Carbomer, Boric Acid, Disodium EDTA, Ethyl Ether, Triethanolamine, Methylparaben, Propylparaben

Questions or comments?
www.BurnBGoneOTC.com